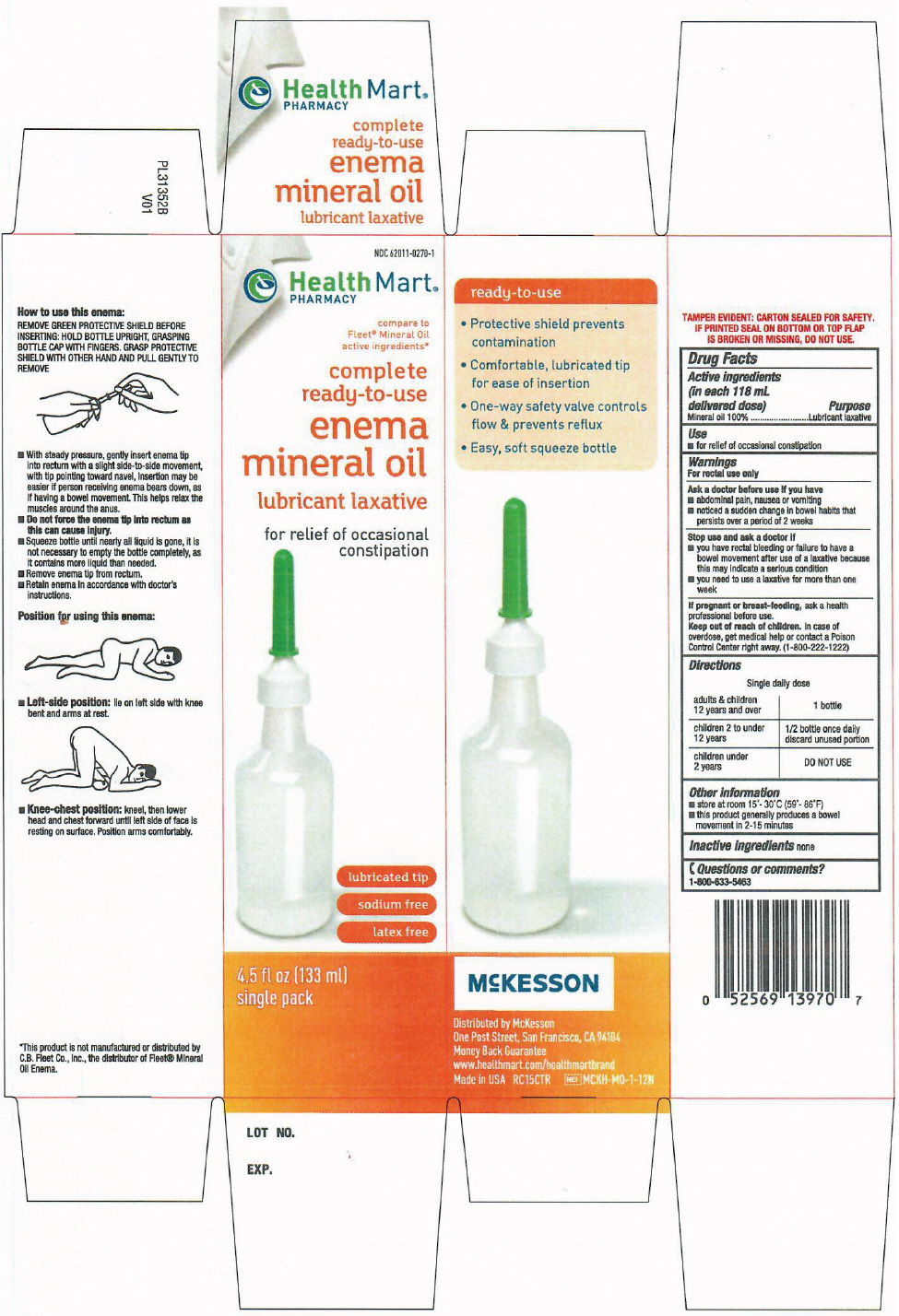 DRUG LABEL: HealthMart Mineral Oil Single 
NDC: 62011-0270 | Form: ENEMA
Manufacturer: Strategic Sourcing Services LLC
Category: otc | Type: HUMAN OTC DRUG LABEL
Date: 20241231

ACTIVE INGREDIENTS: MINERAL OIL 118 g/118 mL

HealthMart® Mineral Oil Enema Single
Laxative

Drug Facts

Active ingredient (in each 118 mL delivered dose)

Mineral Oil 100%

Purpose

Lubricant laxative

Use

- for relief of occasional constipation

Warnings

For rectal use only.

Ask a doctor before use if you have

- abdominal pain, nausea, or vomiting
- a sudden change in bowel habits lasting more than 2 weeks
- already used a laxative for more than 1 week

Stop use and ask a doctor if you have:

- rectal bleeding
- no bowel movement after use

These symptoms may indicate a serious condition.

PREGNANCY OR BREAST FEEDING

If pregnant or breast-feeding, ask a health professional before use.

Keep out of reach of children.

If swallowed, get medical help or contact a Poison Control Center right away: 800-222-1222.

Directions

Single daily dosage

Do not use more unless directed by a doctor. See Warnings.

Adults and children 12 years old and over | 1 bottle
Children 2 to under 12 years old | 1/2 bottle once daily
Children under 2 years | DO NOT USE

Other information

- store at 15 to 30°C (59 to 86°F)
- this product generally produces a bowel movement in 1-5 minutes
- carton sealed for safety. Do not use if safety seal on top flap of carton is torn or missing.

Inactive ingredients

none

Questions or comments?

866-323-0107 or www.natureplex.com

Distributed by McKesson
One Post Street, San Francisco, CA 94104

PRINCIPAL DISPLAY PANEL - 133 ml Bottle Carton

NDC 62011-0270-1

Health Mart®
PHARMACY

compare to
Fleet® Mineral Oil
active ingredients*

complete
ready-to-use
enema
mineral oil

lubricant laxative

for relief of occasional
constipation

lubricated tip
sodium free
latex free

4.5 fl oz (133 ml)
single pack